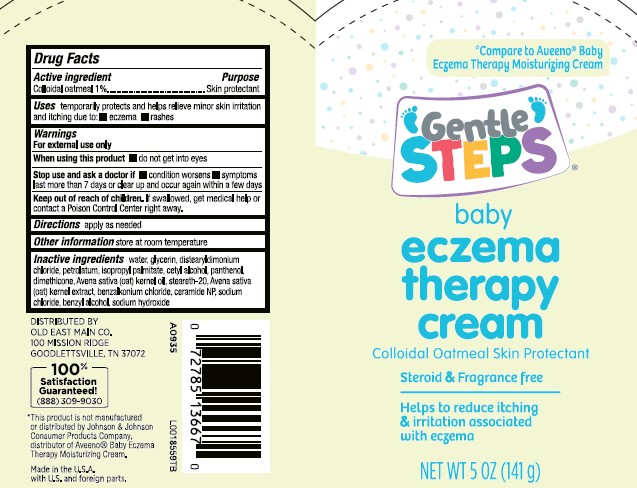 DRUG LABEL: Baby Eczema Therapy
NDC: 55910-803 | Form: CREAM
Manufacturer: Old East Main Co.
Category: otc | Type: HUMAN OTC DRUG LABEL
Date: 20260302

ACTIVE INGREDIENTS: OATMEAL 10.4 kg/1 g
INACTIVE INGREDIENTS: WATER; GLYCERIN; DISTEARYLDIMONIUM CHLORIDE; PETROLATUM; ISOPROPYL PALMITATE; CETYL ALCOHOL; PANTHENOL; DIMETHICONE; OAT KERNEL OIL; STEARETH-20; OAT; BENZALKONIUM CHLORIDE; CERAMIDE NP; SODIUM CHLORIDE; BENZYL ALCOHOL; SODIUM HYDROXIDE

Gentle Steps 601.000/601AB
Baby Eczema Therapy Cream

Active ingredient

Colloidal oatmeal 1%

Purpose

Skin protectant

Uses

temporarily protects and helps relieve minor skin irritation and itching due to:

- eczema
- rashes

Warnings

For external use only

When using this product

- do not get into eyes

Stop use and ask a doctor if

- condition worsens
- symptoms last more than 7 days or clear up and occur again within a few days

Keep out of reach of children.

If swallowed, get medical help or contact a Poison Control Center right away.

Directions

apply as needed

Other information

store at room temperature

Inactive ingredients

water, glycerin, distearyldimonium chloride, petrolatum, isopropl palmitate, cetyl alcohol, panthenol, dimethicone, Avena sativa (oat) kernal oil, steareth-20, Avena sativa (oat) kernal extract, benzalkonium chloride, ceramide NP, sodium chloride, benzyl alcohol, sodium hydroxide

disclaimer

*This product is not manufactured or distributed by Johnson & Johnson Consumer Products Company, distributor of AveenoBaby Eczema Therapy Moisturizing Cream.

Adverse Reactions

DISTRIBUTED BY OLD EAST MAIN CO

100 MISSION RIDGE

GOODLETTSVILLE, TN 37072

100% Satisfaction Guaranteed!

(888) 309-9030

Made in the U.S.A. with U.S. and foreign parts.

principal display panel

*Compare to Aveeno®Baby Eczema Therapy Moisturizing Cream

Gentle Steps®

baby

eczema

therapy

cream

Colloidal Oatmeal Skin Protectant

Steroid & Fragrance Free

Helps to reduce itching and irritation associated with eczema

NET WT 5 OZ (141 g)